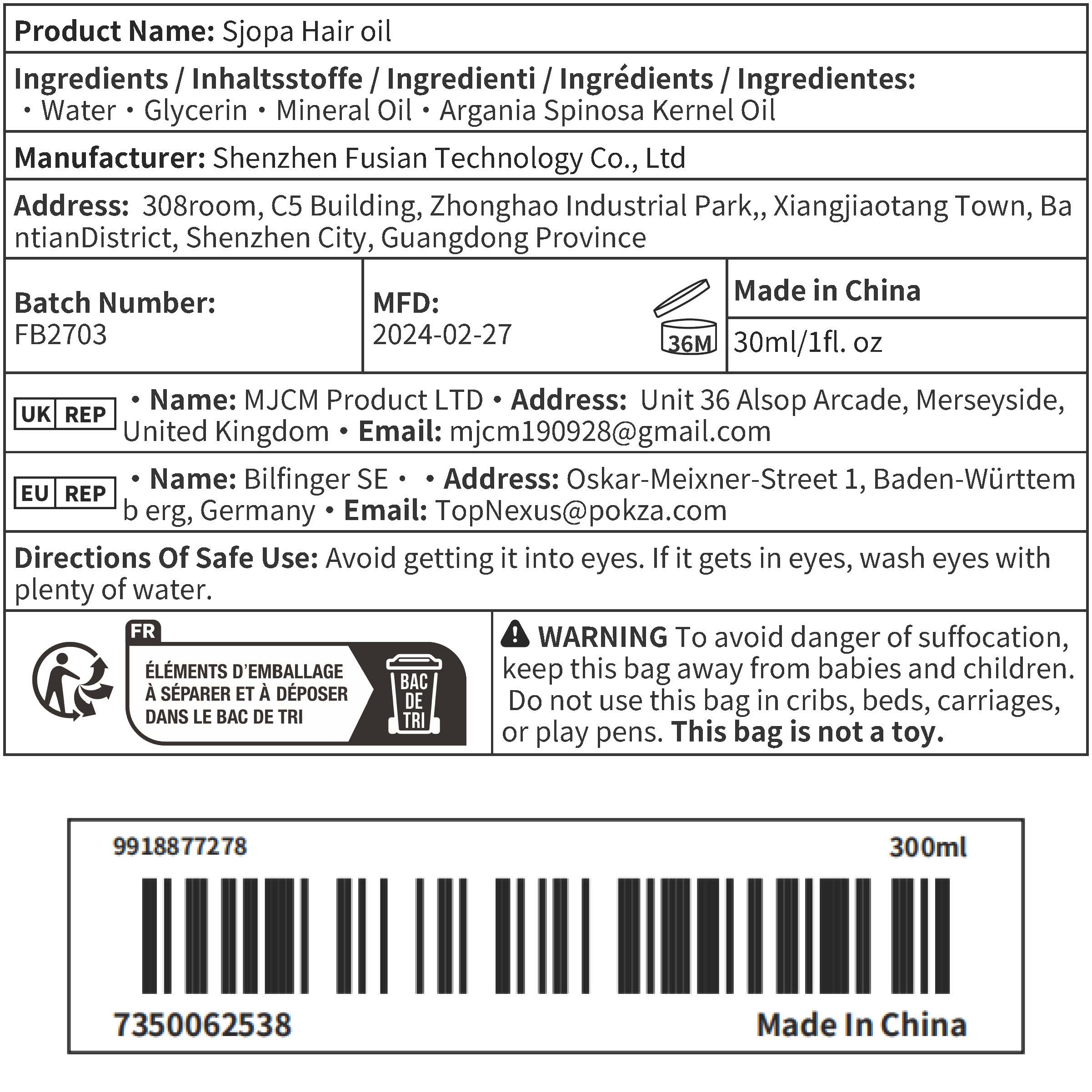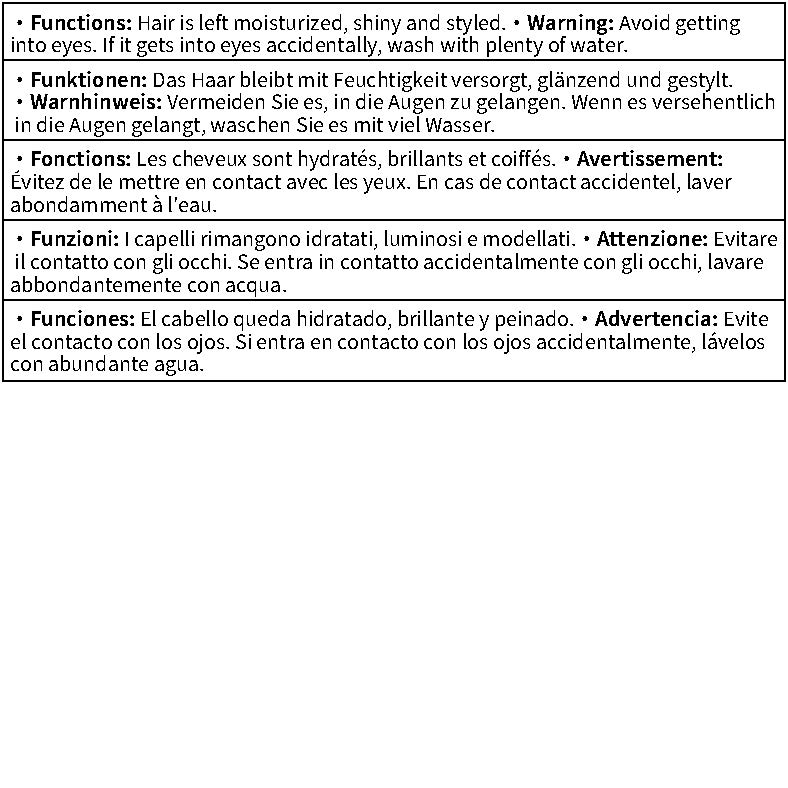 DRUG LABEL: Sjopa Hair oil
NDC: 84775-001 | Form: LIQUID
Manufacturer: Shenzhen Fusian Technology Co., Ltd.
Category: otc | Type: HUMAN OTC DRUG LABEL
Date: 20240819

ACTIVE INGREDIENTS: ARGAN OIL 15 g/30 mL
INACTIVE INGREDIENTS: GLYCERIN; MINERAL OIL; WATER

active

Argania Spinosa Kernel Oil :50%

INACTIVE

Water·Glycerin·MineralOil·

PURPOSE

Hair is left moisturized, shiny and styled

Warning

Avoid gettinginto eyes. lf it gets into eyes accidentally, wash with plenty of water.

DO NOT USE

Avoid gettinginto eyes. lf it gets into eyes accidentally, wash with plenty of water.

WHEN USING

After washing your hair, half dry your hair, rub two to three drops into your hands, then apply evenly to your hair

KEEP OUT OF REACH OF CHILDREN

To avoid danger of suffocation,keep this bag away from babies and children

INDICATIONS AND USAGE

After washing your hair, half dry your hair, rub two to three drops into your hands, then apply evenly to your hair

DOSAGE AND ADMINISTRATION

two to three drops into your hands,